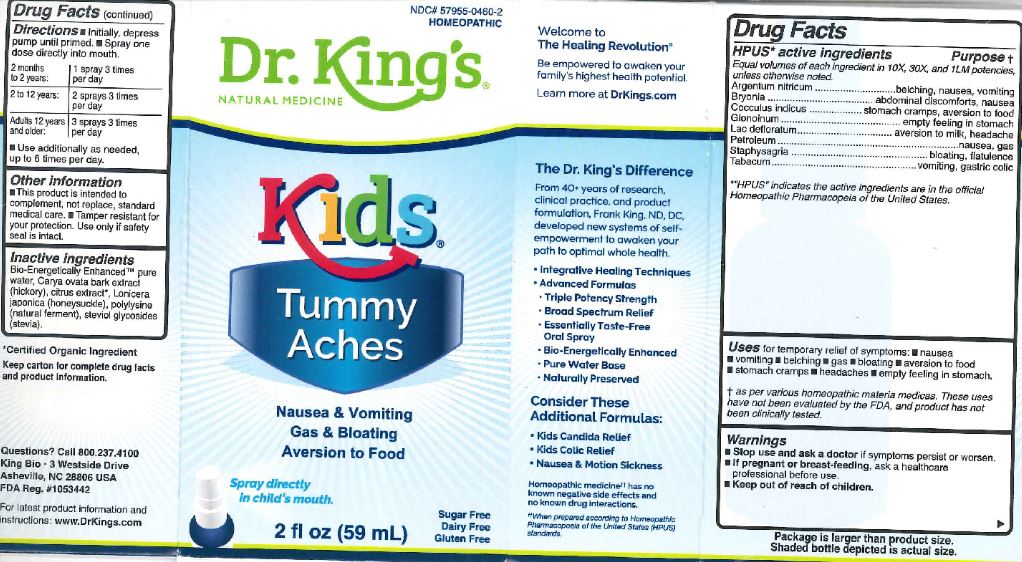 DRUG LABEL: Kids Tummy Aches
NDC: 57955-0460 | Form: LIQUID
Manufacturer: King Bio Inc
Category: homeopathic | Type: HUMAN OTC DRUG LABEL
Date: 20180322

ACTIVE INGREDIENTS: SILVER NITRATE 10 [hp_X]/59 mL; BRYONIA ALBA ROOT 10 [hp_X]/59 mL; ANAMIRTA COCCULUS SEED 10 [hp_X]/59 mL; NITROGLYCERIN 10 [hp_X]/59 mL; SKIM MILK 10 [hp_X]/59 mL; KEROSENE 10 [hp_X]/59 mL; DELPHINIUM STAPHISAGRIA SEED 10 [hp_X]/59 mL; TOBACCO LEAF 10 [hp_X]/59 mL
INACTIVE INGREDIENTS: WATER; CARYA OVATA BARK; CITRUS BIOFLAVONOIDS; LONICERA JAPONICA FLOWER; POLYEPSILON-LYSINE (4000 MW); REBAUDIOSIDE A

Kids Tummy Aches

HPUS Active Ingredients

Argentum nitricum

Bryonia

Cocculus indicus

Glonoinum

Lac defloratum

Petroleum

Staphysagria

Tabacum

Uses

for temporary relief of symptoms:

- nausea
- vomiting
- belching
- gas
- bloating
- aversion to food
- stomach cramps
- headaches
- empty feeling in stomach.

Warnings

- Stop use and ask a doctor, if symptoms persist or worsen.
- If pregnant or breast-feeding, ask a healthcare professional before use.

- Keep out of reach of children

Directions

- Initially, depress pump until primed
- Spray one dose directly into mouth

2 months to 2 years: 1 spray 3 times per day

2 to 12 years: 2 sprays 3 times per day

Adults 12 years and older: 3 sprays 3 times per day

Other Information

- This product is intended to compliment, not replace, standard medical care
- Tamper resistant for your protection. Use only if safety seal is intact.

Inactive Ingredients

Bio-Energeticall Enhanced pure water, Carya ovata bark extract (hickory), citrus extract, Lonicera japonica (honeysuckle), polylysine (natural ferment), steviol glycosides (stevia).

Purpose

Argentum nitricum.......belching, nausea, vomiting

Bryonia.......................abdominal discomforts, nausea

Cocculus indicus..........stomach cramps, aversion to food

Glonoinum..................empty feeling in stomach

Lac defloratum............aversion to milk, headache

Petroleum...................nausea, gas

Staphysagria...............bloating, flatulence

Tabacum....................vomiting, gastric colic